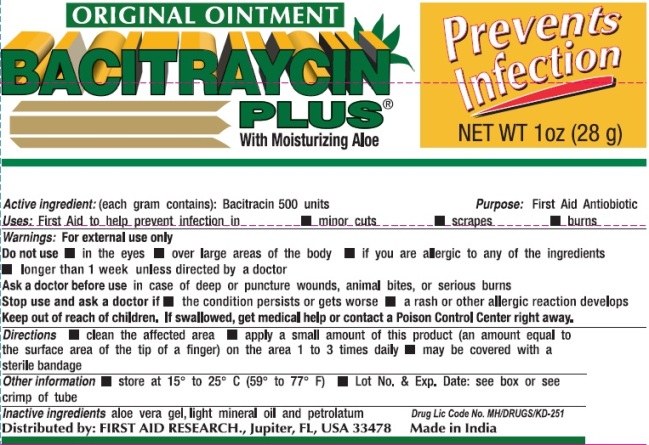 DRUG LABEL: First Aid Bacitraycin Plus Original
NDC: 75983-005 | Form: OINTMENT
Manufacturer: First Aid Research Corp.
Category: otc | Type: HUMAN OTC DRUG LABEL
Date: 20220224

ACTIVE INGREDIENTS: BACITRACIN 500 [USP'U]/1 g
INACTIVE INGREDIENTS: ALOE VERA LEAF; LIGHT MINERAL OIL; PETROLATUM

First Aid Bacitraycin Plus Original Ointment

Active ingredient (each gram contains)

Bacitracin 500 units

Purpose

First Aid Antibiotic

Uses

First Aid to help prevent infection in

- minor cuts
- scrapes
- burns

Warnings

For external use only.

Do not use

- in the eyes
- over large areas of the body
- if you are allergic to any of the ingredients
- longer than 1 week unless directed by a doctor

Ask a doctor before use in case of deep or puncture wounds, animal bites, or serious burns.

Stop use and ask a doctor if

- the condition persists or gets worse
- a rash or other allergic reaction develops

Keep out of reach of children. If swallowed, get medical help or contact a Poison Control Center right away.

Directions

- clean the affected area
- apply a small amount of this product (an amount equal to the surface area of the tip of a finger) on the area 1 to 3 times daily
- may be covered with a sterile bandage

Other information

- store at 15° to 25° C (59° to 77° F)
- Lot No. & Exp. Date: see box or see crimp of tube

Inactive ingredients

aloe vera gel, light mineral oil, and petrolatum

Distributed by:

First Aid Research.

Jupiter, FL 33478

Made in India